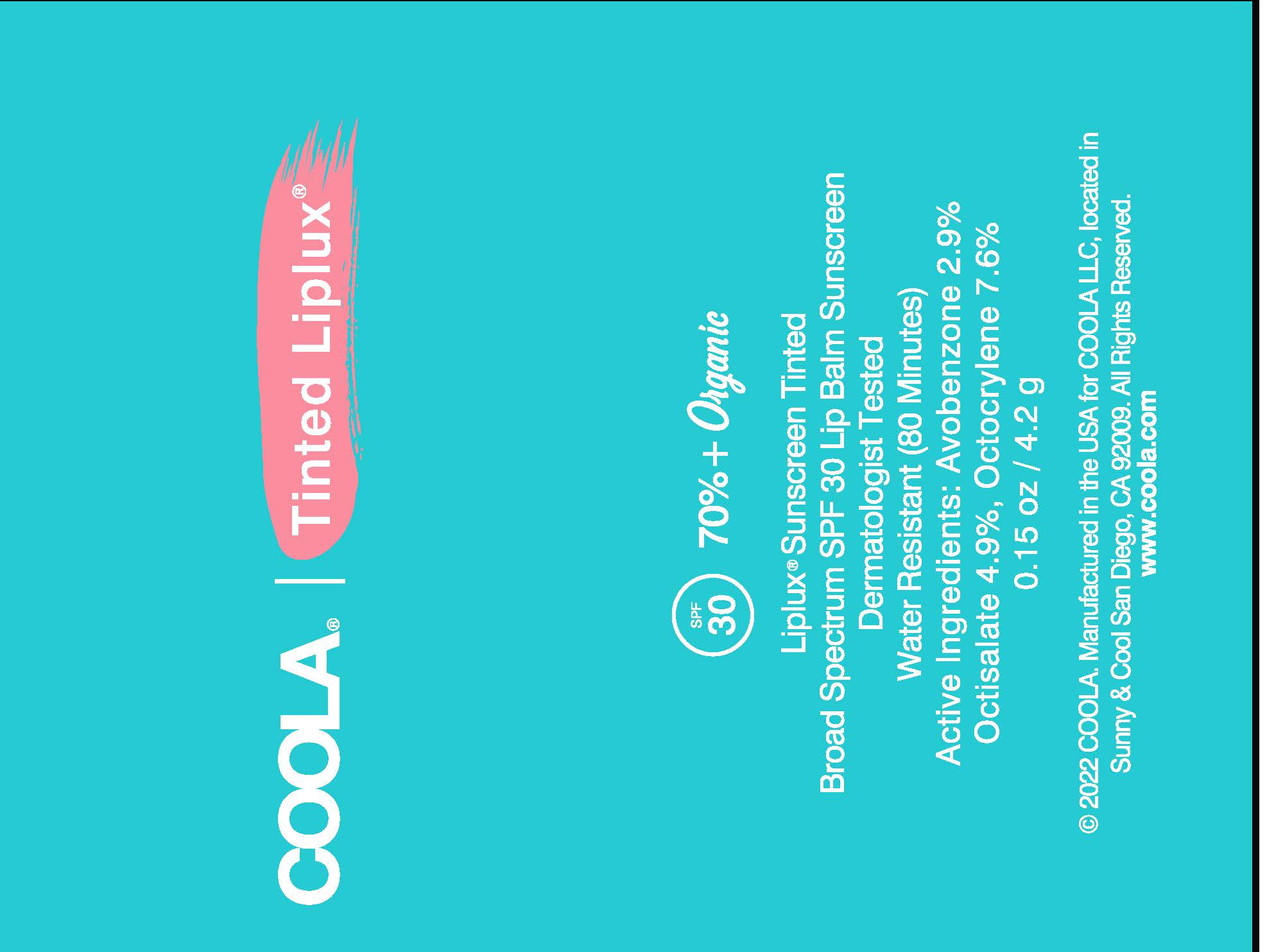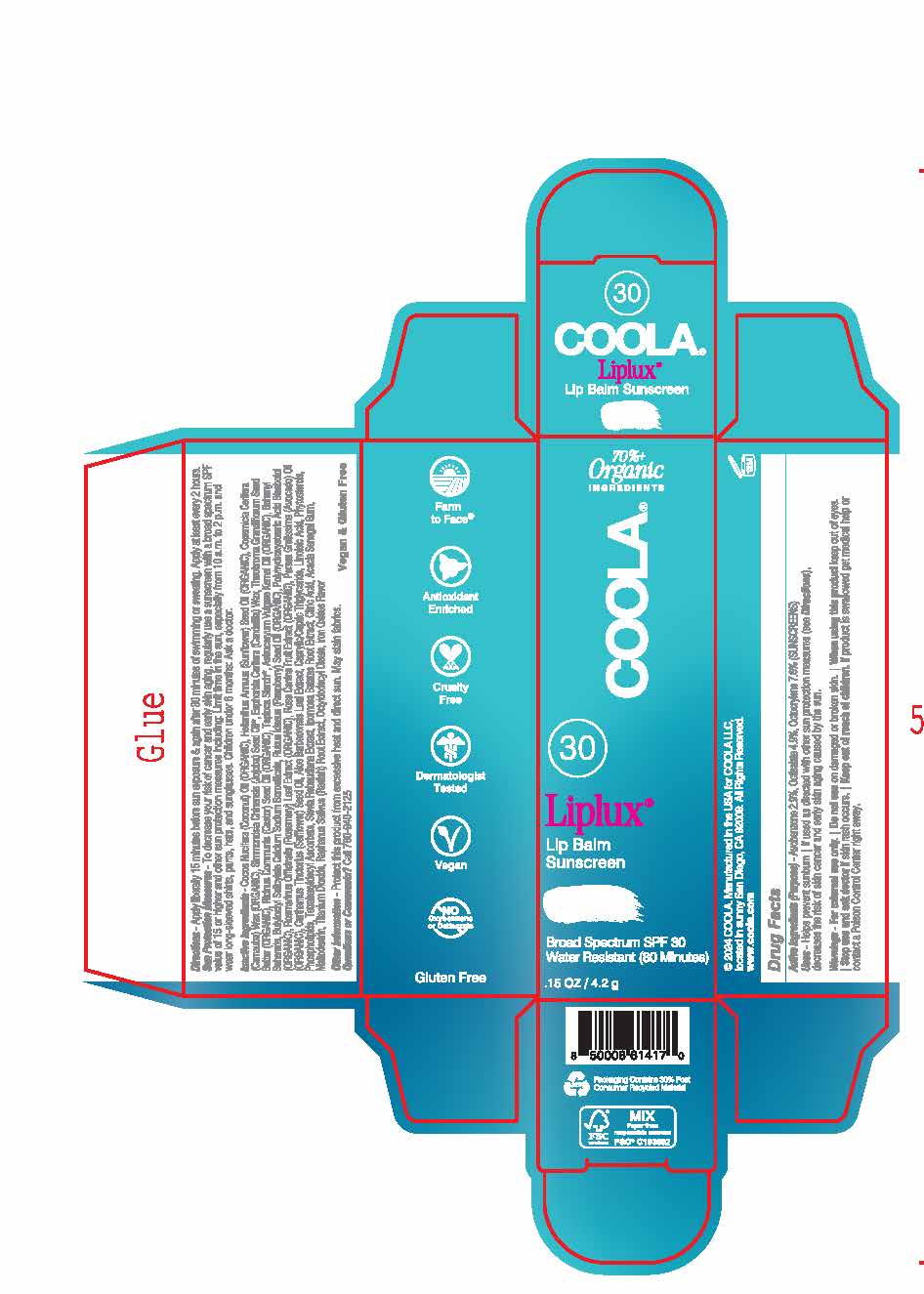 DRUG LABEL: COOLA Classic Liplux Lip Balm SPF 30 Tinted
NDC: 79753-019 | Form: STICK
Manufacturer: COOLA, LLC
Category: otc | Type: HUMAN OTC DRUG LABEL
Date: 20250220

ACTIVE INGREDIENTS: OCTOCRYLENE 7.6 g/100 g; OCTISALATE 4.9 g/100 g; AVOBENZONE 2.9 g/100 g
INACTIVE INGREDIENTS: COCONUT OIL; JOJOBA OIL; ASTROCARYUM VULGARE KERNEL OIL; SOY STEROL; STEVIA REBAUDIUNA LEAF; ROSEMARY; MEDIUM-CHAIN TRIGLYCERIDES; LECITHIN, SOYBEAN; TETRAHEXYLDECYL ASCORBATE; SAFFLOWER OIL; RASPBERRY SEED OIL; OCTYLDODECYL OLEATE; CALCIUM ALUMINUM BOROSILICATE; BUTYLOCTYL SALICYLATE; POLYHYDROXYSTEARIC ACID (2300 MW); ROSA CANINA FRUIT; SWEET POTATO; MALTODEXTRIN; STARCH, TAPIOCA; CITRIC ACID MONOHYDRATE; ACACIA; RADISH; FERRIC OXIDE RED; LINOLEIC ACID; ALOE VERA LEAF; BEHENYL BEHENATE; CARNAUBA WAX; CANDELILLA WAX; CASTOR OIL; LEVOMENOL; AVOCADO OIL; THEOBROMA GRANDIFLORUM SEED BUTTER; SUNFLOWER OIL

COOLA Classic Liplux Lip Balm SPF 30 - Tinted

ACTIVE INGREDIENT

Avobenzone – 2.9%
Octisalate – 4.9%
Octocrylene – 7.6%

PURPOSE

Sunscreen

Uses

- Helps prevent sunburn
- If used as directed with other sun protection measures (see Directions), decreases the risk of skin cancer and early skin aging caused by the sun.

WARNINGS

- For external use only.
- Do not use on damaged or broken skin.
- When using this product keep out of eyes.
- Stop use and ask doctor if skin rash occurs

Keep out of reach of children. If product is swallowed get medical help or contact a Poison Control Center right away.

Directions

- Apply liberally 15 minutes before sun exposure & again after 80 minutes of swimming or sweating.
- Apply at least every 2 hours.
- Sun Protection Measures - To decrease your risk of cancer and early skin aging, regularly use a sunscreen with a broad spectrum SPF value of 15 or higher and other sun protection measures including: Limit time in the sun, especially from 10 a.m. to 2 p.m. and wear long-sleeved shirts, pants, hats, and sunglasses.

INACTIVE INGREDIENT

Cocos Nucifera (Coconut) Oil (ORGANIC), Helianthus Annuus (Sunflower) Seed Oil (ORGANIC), Copernicia Cerifera (Carnauba) Wax (ORGANIC), Simmondsia Chinensis (Jojoba) Seed Oil (ORGANIC), Euphorbia Cerifera (Candelilla) Wax, Theobroma Grandiflorum Seed Butter (ORGANIC), Ricinus Communis (Castor) Seed Oil (ORGANIC), Tapioca Starch (ORGANIC), Astrocaryum Vulgare Kernel Oil (ORGANIC), Behenyl Behenate, Butyloctyl Salicylate, Calcium Sodium Borosilicate, Rubus Idaeus (Raspberry) Seed Oil (ORGANIC), Polyhydroxystearic Acid, Titanium Dioxide, Maltodextrin, Flavor, Bisabolol (ORGANIC), Ipomoea Batatas Tuber Extract, Acacia Senegal Gum, Stevia Rebaudiana Extract, Octyldodecyl Oleate, Iron Oxides, Rosmarinus Officinalis (Rosemary) Leaf Extract (ORGANIC), Citric Acid, Rosa Canina Fruit Extract (ORGANIC), Raphanus Sativus (Radish) Root Extract, Persea Gratissima (Avocado) Oil (ORGANIC), Tetrahexyldecyl Ascorbate, Caprylic/Capric Triglyceride, Tocopherol (ORGANIC), Carthamus Tinctorius (Safflower) Seed Oil, Linoleic Acid, Phospholipids, Phytosterols, Aloe Barbadensis Leaf Extract

OTHER SAFETY INFORMATION

Protect this product from excessive heat and direct sun. May stain fabrics.

QUESTIONS

Call 760-940-2125